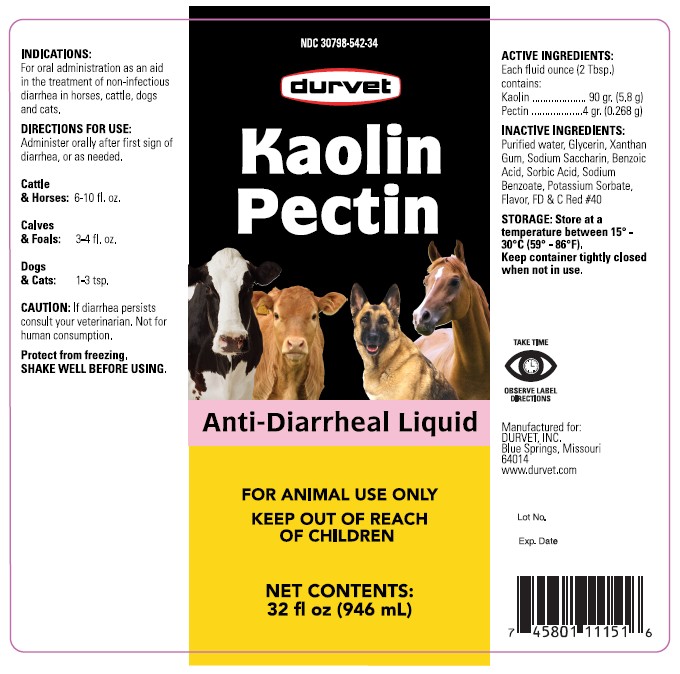 DRUG LABEL: Kaolin Pectin
NDC: 30798-542 | Form: SUSPENSION
Manufacturer: Durvet, Inc.
Category: animal | Type: OTC ANIMAL DRUG LABEL
Date: 20260204

ACTIVE INGREDIENTS: KAOLIN 185 g/946 mL; PECTIN 8.576 g/946 mL
INACTIVE INGREDIENTS: GLYCERIN; XANTHAN GUM; SODIUM SACCHARIN; BENZOIC ACID; SORBIC ACID; SODIUM BENZOATE; POTASSIUM SORBATE; FD&C RED NO. 40; WATER

Kaolin Pectin Anti-Diarrheal Liquid

PURPOSE

Kaolin Pectin

Anti-Diarrheal Liquid

KEEP OUT OF REACH OF CHILDREN

FOR ANIMAL USE ONLY
KEEP OUT OF REACH OF CHILDREN

NET CONTENTS:

32 fl oz (946 mL)

INDICATIONS:

For oral administration as an aid in the treatment of non-infectious diarrhea in horses, cattle, dogs and cats.

DIRECTIONS FOR USE:

Administer orally after first sign of diarrhea, or as needed.

Cattle & Horses: 6-10 fl oz
Calves & Foals: 3-4 fl oz
Dogs & Cats: 1-3 tsp

CAUTION:

If diarrhea persists consult your veterinarian. Not for human consumption.
Protect from freezing.
SHAKE WELL BEFORE USING.

ACTIVE INGREDIENTS:

Each fluid ounce (2 Tbs) contains:
Kaolin ............................................. 90 gr. (5.8 g)
Pectin ............................................. 4 gr. (0.268 g)

INACTIVE INGREDIENTS:

Purified water, Glycerin, Xanthan Gum, Sodium Saccharin, Benzoic Acid, Sorbic Acid, Sodium Benzoate, Potassium Sorbate, Flavor, FD & C Red #40.

STORAGE:

Store at a temperature between 15º - 30ºC (59º - 86ºF).

Keep container tightly closed when not in use.

INFORMATION FOR OWNERS/CAREGIVERS

Manufactured for:
DURVET, INC.
Blue Springs, Missouri 64014
www.durvet.com

PACKAGE LABEL

32 fl oz (946 mL)